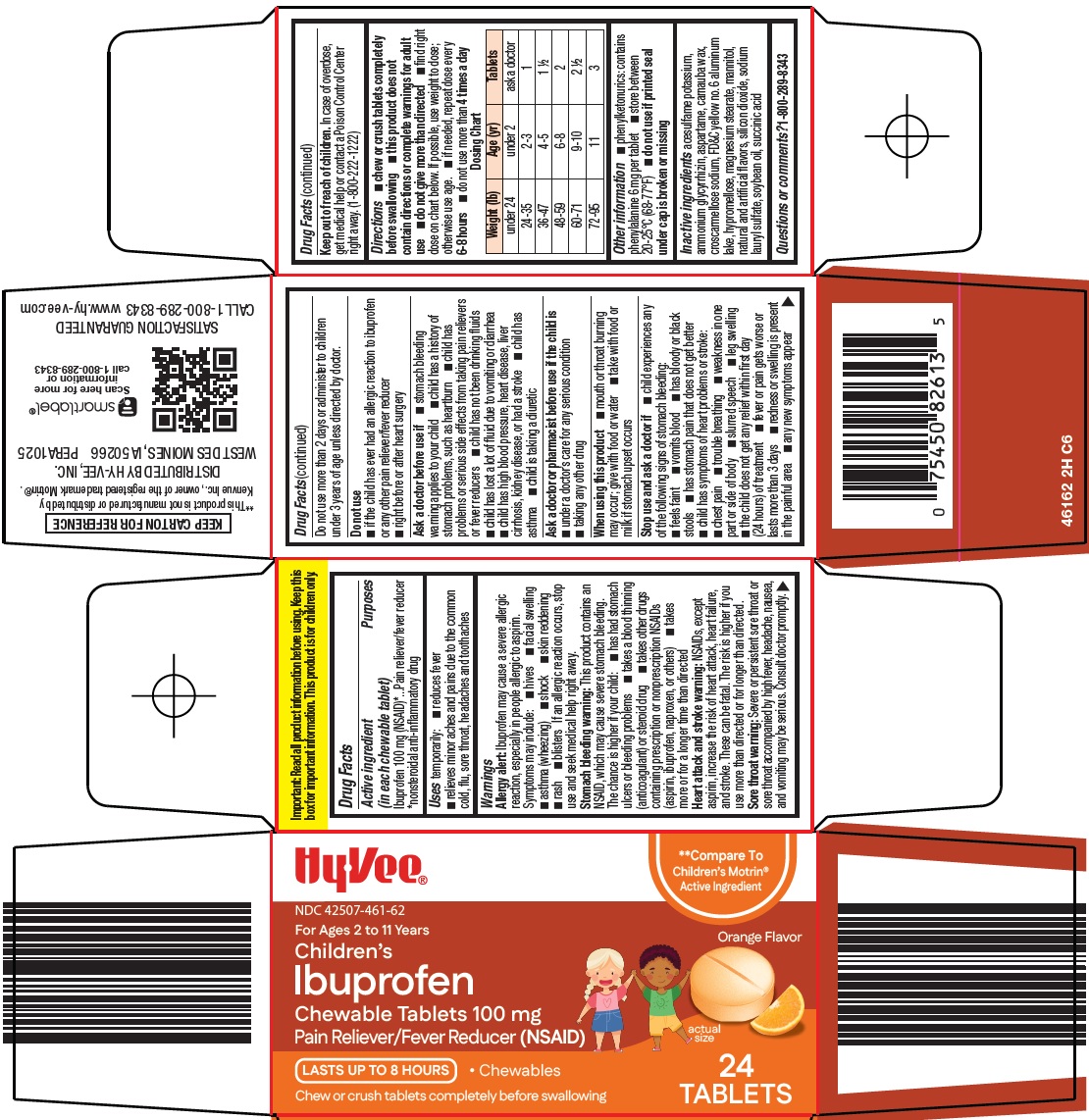 DRUG LABEL: ibuprofen
NDC: 42507-461 | Form: TABLET, CHEWABLE
Manufacturer: HyVee Inc
Category: otc | Type: HUMAN OTC DRUG LABEL
Date: 20260113

ACTIVE INGREDIENTS: IBUPROFEN 100 mg/1 1
INACTIVE INGREDIENTS: ACESULFAME POTASSIUM; AMMONIUM GLYCYRRHIZATE; ASPARTAME; CARNAUBA WAX; CROSCARMELLOSE SODIUM; FD&C YELLOW NO. 6 ALUMINUM LAKE; HYPROMELLOSE, UNSPECIFIED; MAGNESIUM STEARATE; MANNITOL; SILICON DIOXIDE; SODIUM LAURYL SULFATE; SOYBEAN OIL; SUCCINIC ACID

Hy-Vee, Inc. Children’s Ibuprofen Drug Facts

Active ingredient (in each chewable tablet)

Ibuprofen 100 mg (NSAID)*

*nonsteroidal anti-inflammatory drug

Purposes

Pain reliever/fever reducer

Uses

temporarily:

1. reduces fever
2. relieves minor aches and pains due to the common cold, flu, sore throat, headaches and toothaches

Warnings

Allergy alert: Ibuprofen may cause a severe allergic reaction, especially in people allergic to aspirin. Symptoms may include:

1. hives
2. facial swelling
3. asthma (wheezing)
4. shock
5. skin reddening
6. rash
7. blisters

If an allergic reaction occurs, stop use and seek medical help right away.

Stomach bleeding warning: This product contains an NSAID, which may cause severe stomach bleeding. The chance is higher if your child:

1. has had stomach ulcers or bleeding problems
2. takes a blood thinning (anticoagulant) or steroid drug
3. takes other drugs containing prescription or nonprescription NSAIDs (aspirin, ibuprofen, naproxen, or others)
4. takes more or for a longer time than directed

Sore throat warning: Severe or persistent sore throat or sore throat accompanied by high fever, headache, nausea, and vomiting may be serious. Consult doctor promptly. Do not use more than 2 days or administer to children under 3 years of age unless directed by doctor.

Do not use

1. if the child has ever had an allergic reaction to any other pain reliever/fever reducer
2. right before or after heart surgery

Ask a doctor before use if

1. stomach bleeding warning applies to your child
2. child has a history of stomach problems, such as heartburn
3. child has problems or serious side effects from taking pain relievers or fever reducers
4. child has not been drinking fluids
5. child has lost a lot of fluid due to vomiting or diarrhea
6. child has high blood pressure, heart disease, liver cirrhosis, kidney disease, or had a stroke
7. child has asthma
8. child is taking a diuretic

Ask a doctor or pharmacist before use if the child is

1. under a doctor’s care for any serious condition
2. taking any other drug

When using this product

1. mouth or throat burning may occur; give with food or water
2. take with food or milk if stomach upset occurs

Stop use and ask a doctor if

1. child experiences any of the following signs of stomach bleeding:
2. feels faint
3. vomits blood
4. has bloody or black stools
5. has stomach pain that does not get better
6. child has symptoms of heart problems or stroke:
7. chest pain
8. trouble breathing
9. weakness in one part or side of body
10. slurred speech
11. leg swelling
12. the child does not get any relief within the first day (24 hours) of treatment
13. fever or pain gets worse or lasts more than 3 days
14. redness or swelling is present in the painful area
15. any new symptoms appear

Keep out of reach of children.

In case of overdose, get medical help or contact a Poison Control Center right away. (1-800-222-1222)

Directions

1. chew or crush tablets completely before swallowing
2. this product does not contain directions or complete warnings for adult use
3. do not give more than directed
4. find right dose on chart below. If possible, use weight to dose; otherwise use age.
5. if needed, repeat dose every 6-8 hours
6. do not use more than 4 times a day

Dosing Chart
Weight (lb) | Age (yr) | Tablets
under 24 | under 2 | ask a doctor
24-35 | 2-3 | 1
36-47 | 4-5 | 1 ½
48-59 | 6-8 | 2
60-71 | 9-10 | 2 ½
72-95 | 11 | 3

Other information

1. phenylketonurics: contains phenylalanine 6 mg per tablet
2. store between 20-25°C (68-77°F)
3. do not use if printed seal under cap is broken or missing

Inactive ingredients

acesulfame potassium, ammonium glycyrrhizin, aspartame, carnauba wax, croscarmellose sodium, FD&C yellow no. 6 aluminum lake, hypromellose, magnesium stearate, mannitol, natural and artificial flavors, silicon dioxide, sodium lauryl sulfate, soybean oil, succinic acid

Questions or comments?

1-800-289-8343

Principal Display Panel

Hy•Vee®

Compare To Children’s Motrin® Active Ingredient

For Ages 2 to 11 Years

Orange Flavor

Children’s Ibuprofen

Chewable Tablets 100 mg

Pain Reliever/Fever Reducer (NSAID)

actual size

LASTS UP TO 8 HOURS

• Chewables

Chew or crush tablets completely before swallowing

24 TABLETS